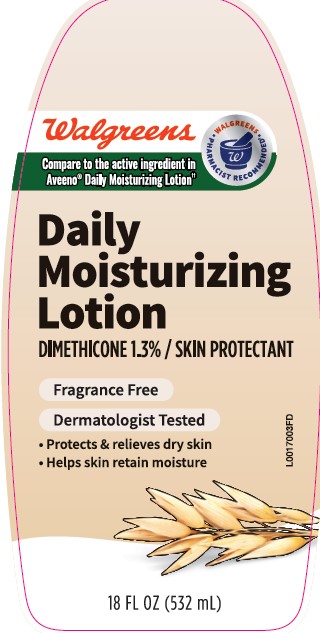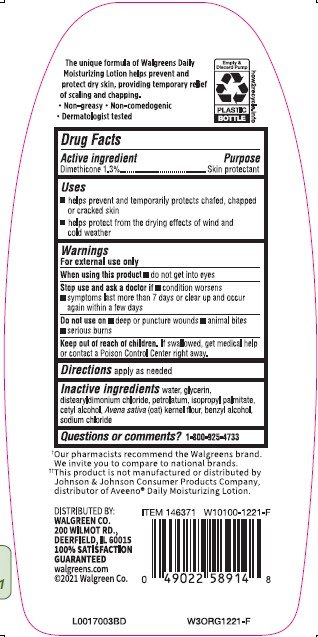 DRUG LABEL: Daily Moisturizing
NDC: 0363-0619 | Form: LOTION
Manufacturer: Walgreen Co.
Category: otc | Type: HUMAN OTC DRUG LABEL
Date: 20260212

ACTIVE INGREDIENTS: DIMETHICONE 13 mg/1 g
INACTIVE INGREDIENTS: WATER; GLYCERIN; DISTEARYLDIMONIUM CHLORIDE; PETROLATUM; ISOPROPYL PALMITATE; CETYL ALCOHOL; OATMEAL; BENZYL ALCOHOL; SODIUM CHLORIDE

Walgreens 619.003/619AC rev 2
Daily moisturizing lotion

Claims

The unique formula of Walgreens Daily Moisturizing Lotion helps prevent and protect dry skin, providing temporary relief of scaling and chapping.

- Non-greasy
- Non-comedogenic
- Dermatologist tested

Active ingredient

Dimethicone 1.3%

Purpose

Skin protectant

Uses

- helps prevent and temporarily protects chafed, chapped, or cracked skin
- helps protect from the drying effects of wind and cold weather

Warnings

For external use only

When using this product

- do not get into eyes

Stop use and ask a doctor if

- condition worsens
- symptoms last more than 7 days or clear up and occur again within a few days

Do not use on

- deep or puncture wounds
- animal bites
- serious burns

Keep out of reach of children.

If swallowed, get medical help or contact a Poison Control Center right away.

Directions

apply as needed

Inactive ingredients

water, glycerin, distearyldimonium chloride, petrolatum, isopropyl palmitate, cetyl alcohol, Avena sativa (oat) kernel flour, benzyl alcohol, sodium chloride

Questions or comments?

1-800-925-4733

Claims

†Our pharmacists recommend the Walgreens brand. We invite you to compare to national brands.

Disclaimer

††This product is not manufactured or distributed by Johnson & Johnson Prodcuts Company, distributor of Aveeno®Active Daily Moisturizing Lotion.

Adverse reactions

DISTRIBUTED BY:

WALGREEN CO.

200 WILMOT ROAD

DEERFIELD, IL 60015

100% SATISFACTION GUARANTEED

walgreens.com

©2021 Walgreen Co.

Empty & Discard Pump

PLASTIC BOTTLE

how2recycle.info

Principal display panel

Walgreens

Walgreens Pharmacist Recommended†

Compare to active ingredient in Aveeno®Daily Moisturizing Lotion††

Daily

Moisturizing

Lotion

DIMETHICONE 1.3% / SKIN PROTECTANT

FRAGRANCE FREE

DERMATOLOGIST TESTED

- Protects & relieves dry skin
- Helps skin retain moisture

18 FL OZ (532 mL)